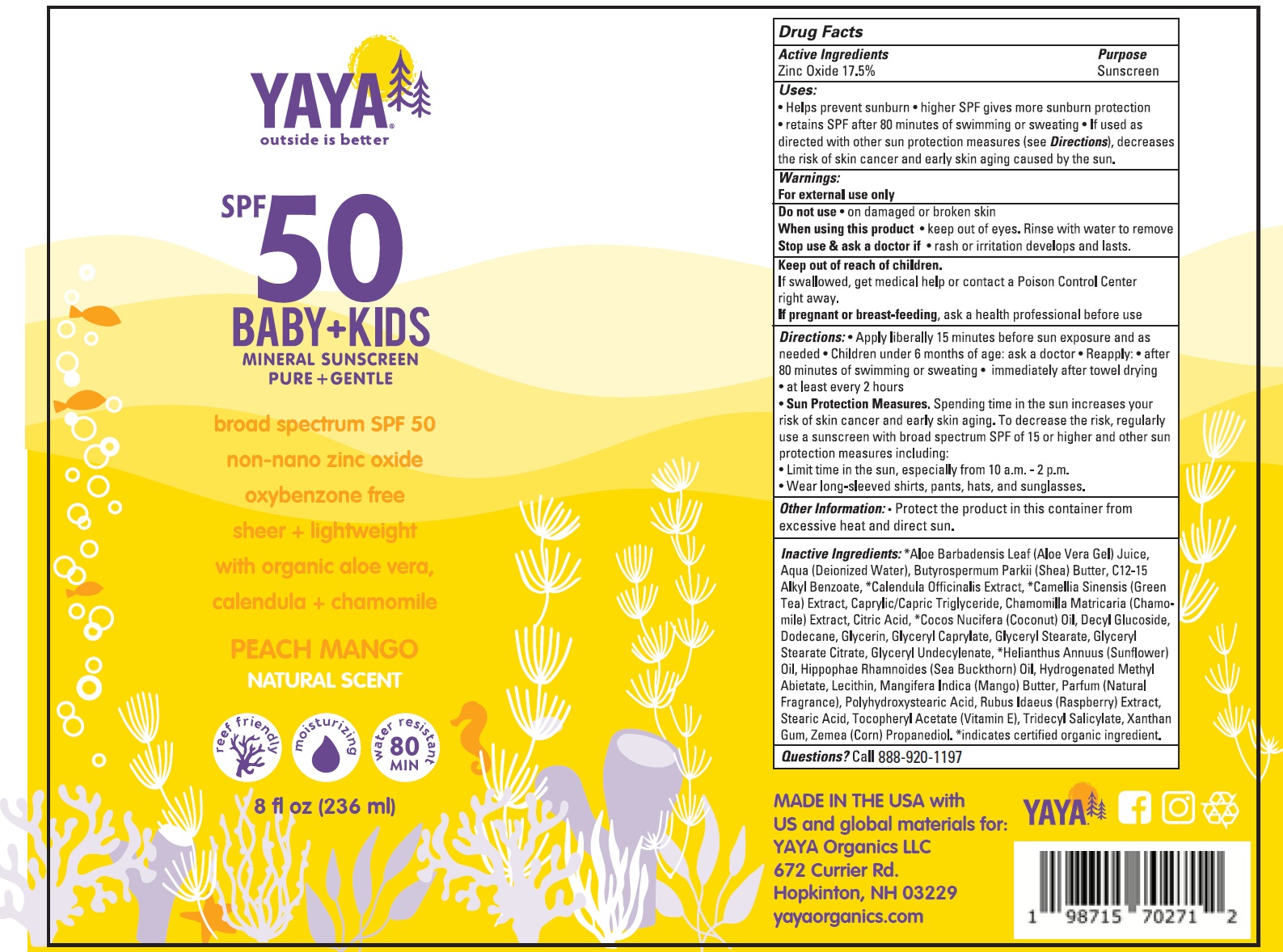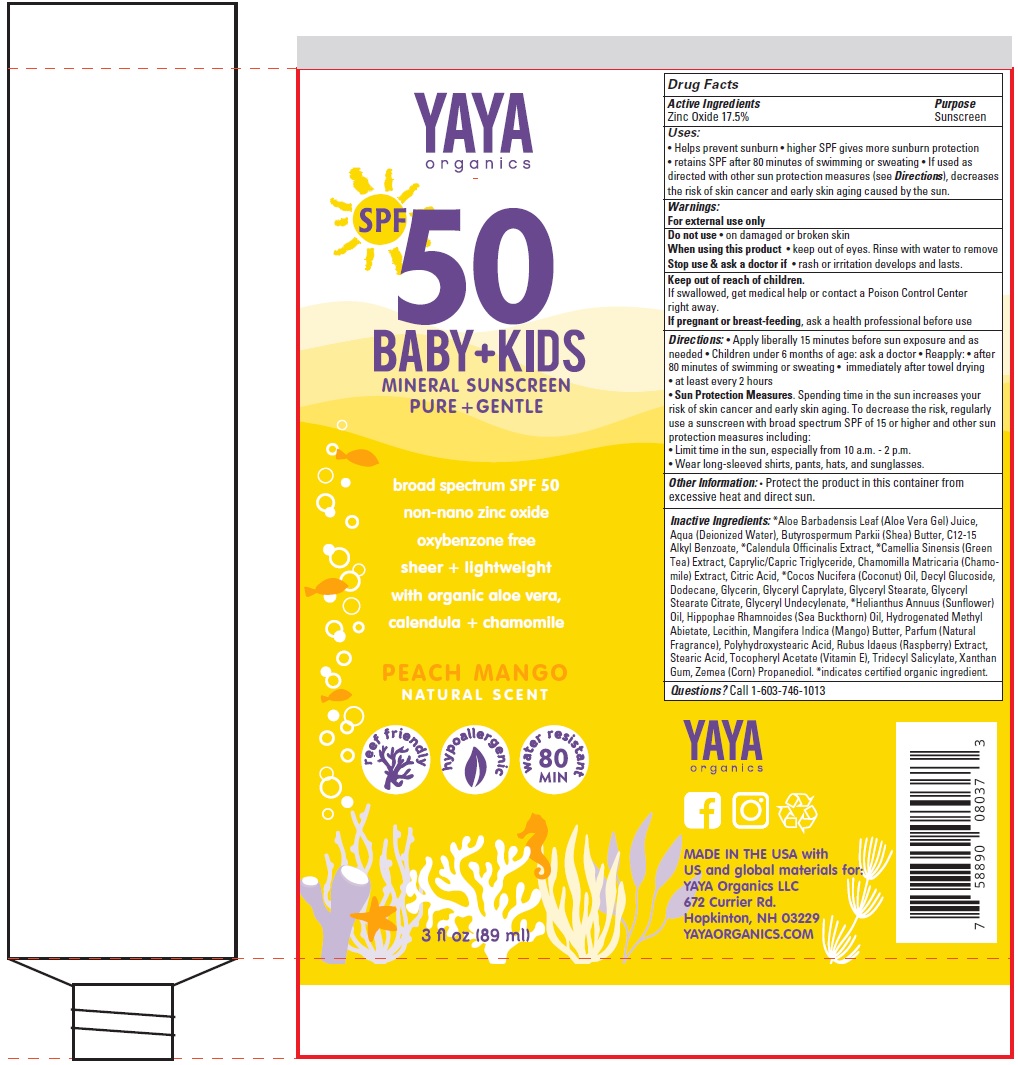 DRUG LABEL: YAYA Organics SPF-50 Baby Kids Mineral Sunscreen
NDC: 82526-268 | Form: CREAM
Manufacturer: YAYA ORGANICS L.L.C.
Category: otc | Type: HUMAN OTC DRUG LABEL
Date: 20250422

ACTIVE INGREDIENTS: ZINC OXIDE 175 mg/1 mL
INACTIVE INGREDIENTS: ALOE VERA LEAF; WATER; SHEA BUTTER; ALKYL (C12-15) BENZOATE; CALENDULA OFFICINALIS FLOWER; GREEN TEA LEAF; MEDIUM-CHAIN TRIGLYCERIDES; CHAMOMILE; CITRIC ACID MONOHYDRATE; COCONUT OIL; DECYL GLUCOSIDE; DODECANE; GLYCERIN; GLYCERYL MONOCAPRYLATE; GLYCERYL MONOSTEARATE; GLYCERYL STEARATE CITRATE; HELIANTHUS ANNUUS FLOWERING TOP; HYDROGENATED METHYL ABIETATE; MANGO; RASPBERRY; STEARIC ACID; .ALPHA.-TOCOPHEROL ACETATE; TRIDECYL SALICYLATE; XANTHAN GUM; CORN

YAYA Organics SPF-50 Baby + Kids Mineral Sunscreen

Active Ingredients

Zinc Oxide 17.5%

Purpose

Sunscreen

Uses:

• Helps prevent sunburn • higher SPF gives more sunburn protection • retains SPF after 80 minutes of swimming or sweating • If used as directed with other sun protection measures (see Directions), decreases the risk of skin cancer and early skin aging caused by the sun.

Warnings:

For external use only

Do not use

• on damaged or broken skin

When using this product

- keep out of eyes. Rinse with water to remove

Stop use & ask a doctor if

• rash or irritation develops and lasts.

Keep out of reach of children.

If swallowed, get medical help or contact a Poison Control Center right away.

If pregnant or breast-feeding,

ask a health professional before use

Directions:

• Apply liberally 15 minutes before sun exposure and as needed • Children under 6 months of age: ask a doctor • Reapply: • after 80 minutes of swimming or sweating • immediately after towel drying • at least every 2 hours • . Spending time in the sun increases your risk of skin cancer and early skin aging. To decrease the risk, regularly use a sunscreen with broad spectrum SPF of 15 or higher and other sun protection measures including: • Limit time in the sun, especially from 10 a.m. - 2 p.m. • Wear long-sleeved shirts, pants, hats, and sunglasses.
Sun Protection Measures

Other Information:

• Protect the product in this container from excessive heat and direct sun.

Inactive Ingredients:

*Aloe Barbadensis Leaf (Aloe Vera Gel) Juice, Aqua (Deionized Water), Butyrospermum Parkii (Shea) Butter, C12-15 Alkyl Benzoate, *Calendula Officinalis Extract, *Camellia Sinensis (Green Tea) Extract, Caprylic/Capric Triglyceride, Chamomilla Matricaria (Chamomile) Extract, Citric Acid, *Cocos Nucifera (Coconut) Oil, Decyl Glucoside, Dodecane, Glycerin, Glyceryl Caprylate, Glyceryl Stearate, Glyceryl Stearate Citrate, Glyceryl Undecylenate, *Helianthus Annuus (Sunflower) Oil, Hippophae Rhamnoides (Sea Buckthorn) Oil, Hydrogenated Methyl Abietate, Lecithin, Mangifera Indica (Mango) Butter, Parfum (Natural Fragrance), Polyhydroxystearic Acid, Rubus Idaeus (Raspberry) Extract, Stearic Acid, Tocopheryl Acetate (Vitamin E), Tridecyl Salicylate, Xanthan Gum, Zemea (Corn) Propanediol. *indicates certified organic ingredient.

Questions?

Call 1-603-746-1013